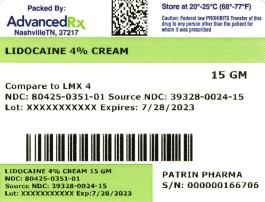 DRUG LABEL: Lidocaine
NDC: 80425-0351 | Form: CREAM
Manufacturer: Advanced Rx Pharmacy of Tennessee, LLC
Category: otc | Type: HUMAN OTC DRUG LABEL
Date: 20241231

ACTIVE INGREDIENTS: LIDOCAINE 40 mg/1 g
INACTIVE INGREDIENTS: BENZYL ALCOHOL; CARBOMER HOMOPOLYMER TYPE C (ALLYL PENTAERYTHRITOL CROSSLINKED); HYDROGENATED SOYBEAN LECITHIN; POLYSORBATE 80; PROPYLENE GLYCOL; WATER; TROLAMINE; .ALPHA.-TOCOPHEROL ACETATE

Lidocaine Cream

Drug Facts

Active Ingredient

Lidocaine 4% w/w

Purpose

Topical anesthetic

Uses

temporarily relieves pain and itching due to

- minor cuts
- minor scrapes
- minor burns
- sunburn
- minor skin irritation
- insect bites

Directions

- Adult and children 2 years and older: Apply externally to the affected area up to 3 to 4 times a day.
- Children under 2 years of age: Consult a doctor.

Warnings

For external use only.

Do not use

- in or near the eyes
- in large quantities, particularly over raw or blistered areas

Stop use and ask a doctor if

- allergic reaction occurs
- condition worsens or does not improve within 7 days
- symptoms clear up and return within a few days
- redness, irritation, swelling, pain or other symptoms begin or increase

Keep out of reach of children. If swallowed, get medical help or contact a Poison Control Center right away.

Other Information

- May be applied under occlusive dressing.
- Store at room temperature, 20–25°C (68–77°F) Excursions permitted 15–30°C (59–86°F) [see USP Controlled Room Temperature].

Inactive ingredients

Benzyl Alcohol, Carbopol 940, Hydrogenated Lecithin, Polysorbate 80, Propylene Glycol, Purified Water, Trolamine and Vitamin E Acetate.

Questions?

Call 800-936-3088

How Supplied/Storage and Handling

Lidocaine 4% Cream is supplied in:

15g tube NDC: 80425-0351-01

Store at room temperature, 20–25°C (68–77°F) Excursions permitted 15–30°C (59–86°F) [see USP Controlled Room Temperature].